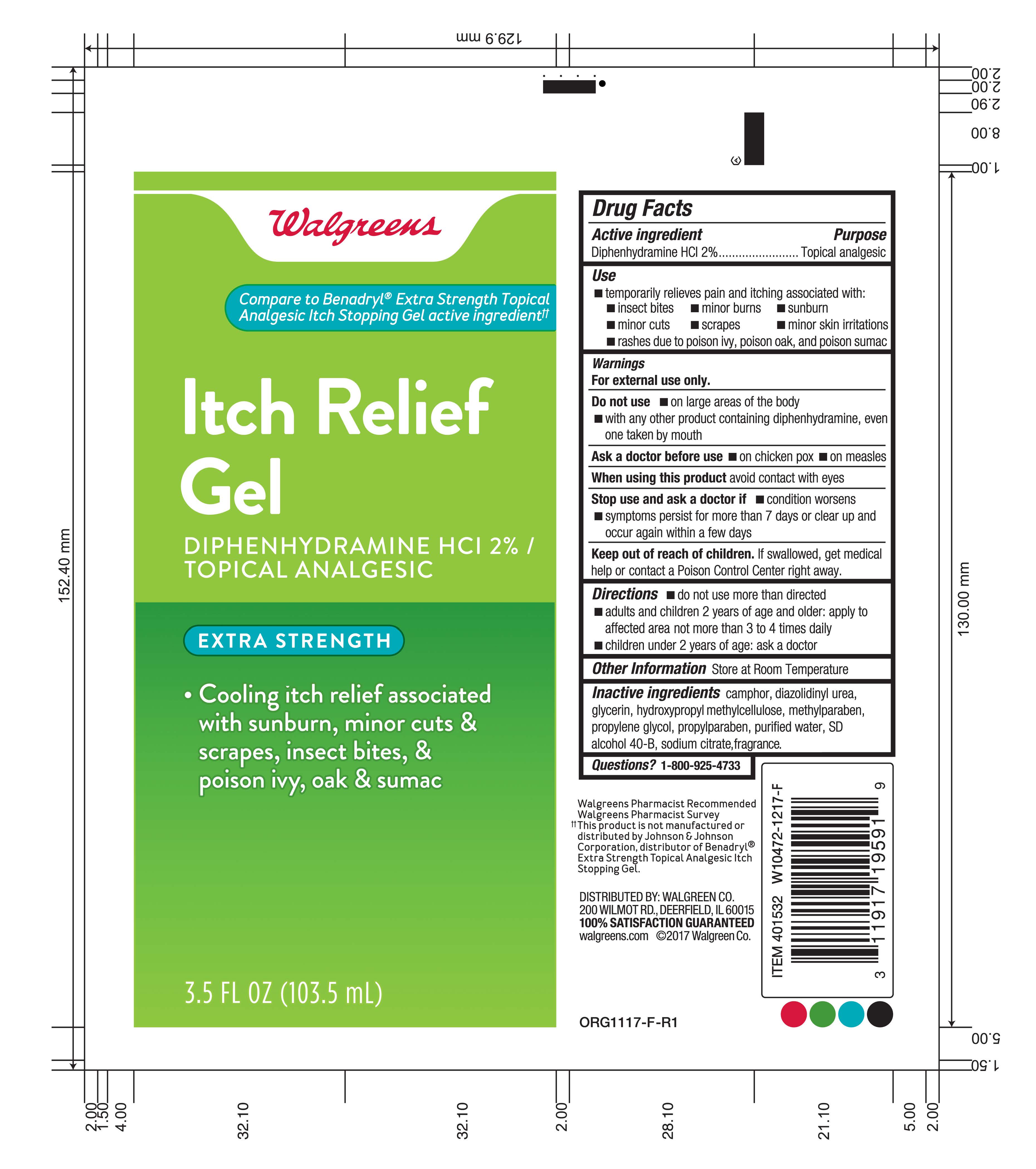 DRUG LABEL: Itch Relief Gel
NDC: 0363-0353 | Form: GEL
Manufacturer: Walgreens
Category: otc | Type: HUMAN OTC DRUG LABEL
Date: 20260115

ACTIVE INGREDIENTS: DIPHENHYDRAMINE HYDROCHLORIDE 2 mg/100 mL
INACTIVE INGREDIENTS: WATER; PROPYLENE GLYCOL; GLYCERIN; DIAZOLIDINYL UREA; SODIUM CITRATE; METHYLPARABEN; PROPYLPARABEN; CAMPHOR (SYNTHETIC); ALCOHOL; HYPROMELLOSE 2208 (15000 MPA.S)

Walgreens Itch Relief Gel

Active ingredient

Diphenhydramine HCL 2%

Purpose

Topical Analgesic

Use

Temporarily relieves pain and itching associated with: insect bites, minor burns, sunburn, minor cuts, scrapes, minor skin irritations, rashes due to poison ivy, poison oak, and poison sumac

Warnings

For external use only.

Do not use:

on large areas of the body,

with any other product containing diphenhydramine, even one taken by mouth

Ask a doctor before use

on chicken pox,

on measles

When using this product

avoid contact with eyes

Stop use and ask a doctor if

condition worsens, symptoms persist for more than 7 days or clear up and occur again within a few days

Keep out of reach of children.

If swallowed, get medical help or contact a Poison Control Center right away.

Directions

Do not use more than directed.

Adults and children 2 years of age and older: apply to affected area not more than 3 to 4 times daily.

Other information

Store at room temperature

Inactive ingredients

camphor, diazolidinyl urea, glycerin, hydroxypropyl methylcellulose, methylparaben, propylene glycol, propylparaben, purified water, SD alcohol 40-B, sodium citrate

Questions?

1-800-925-4733

Directions

Apply to affected area not more thatn 3 to 4 times daily